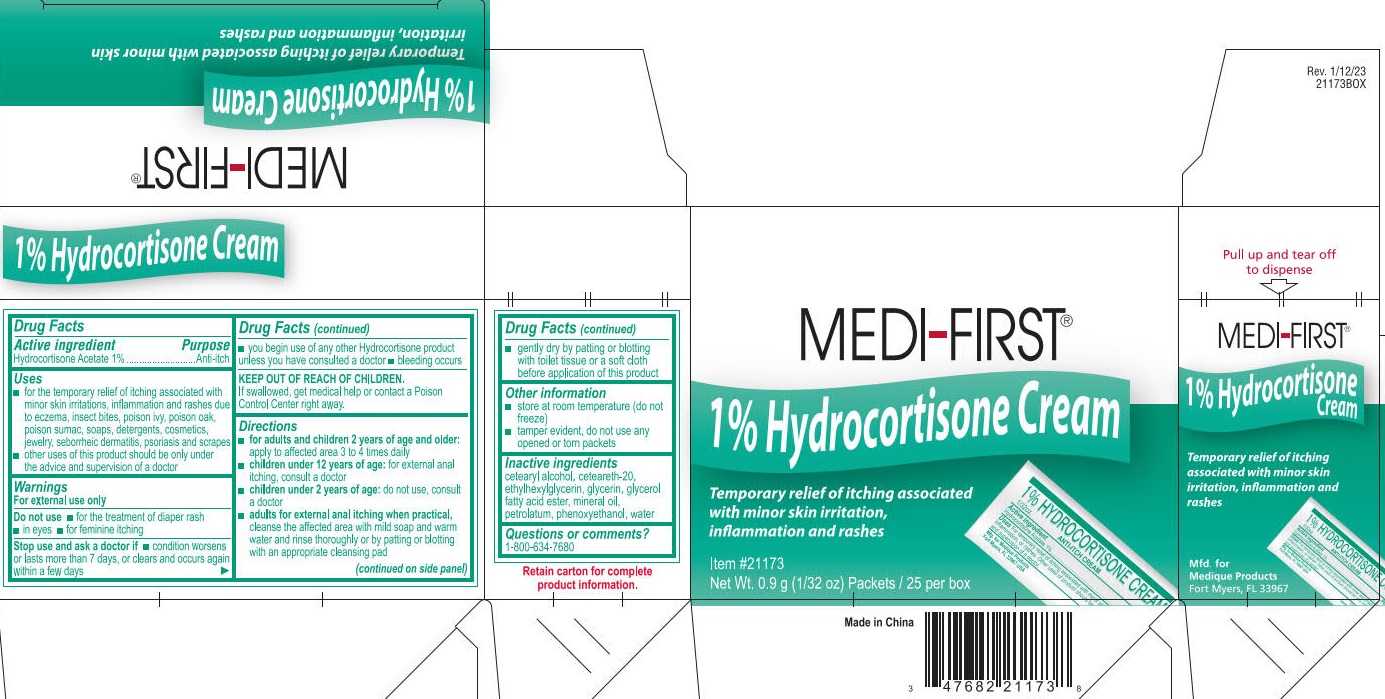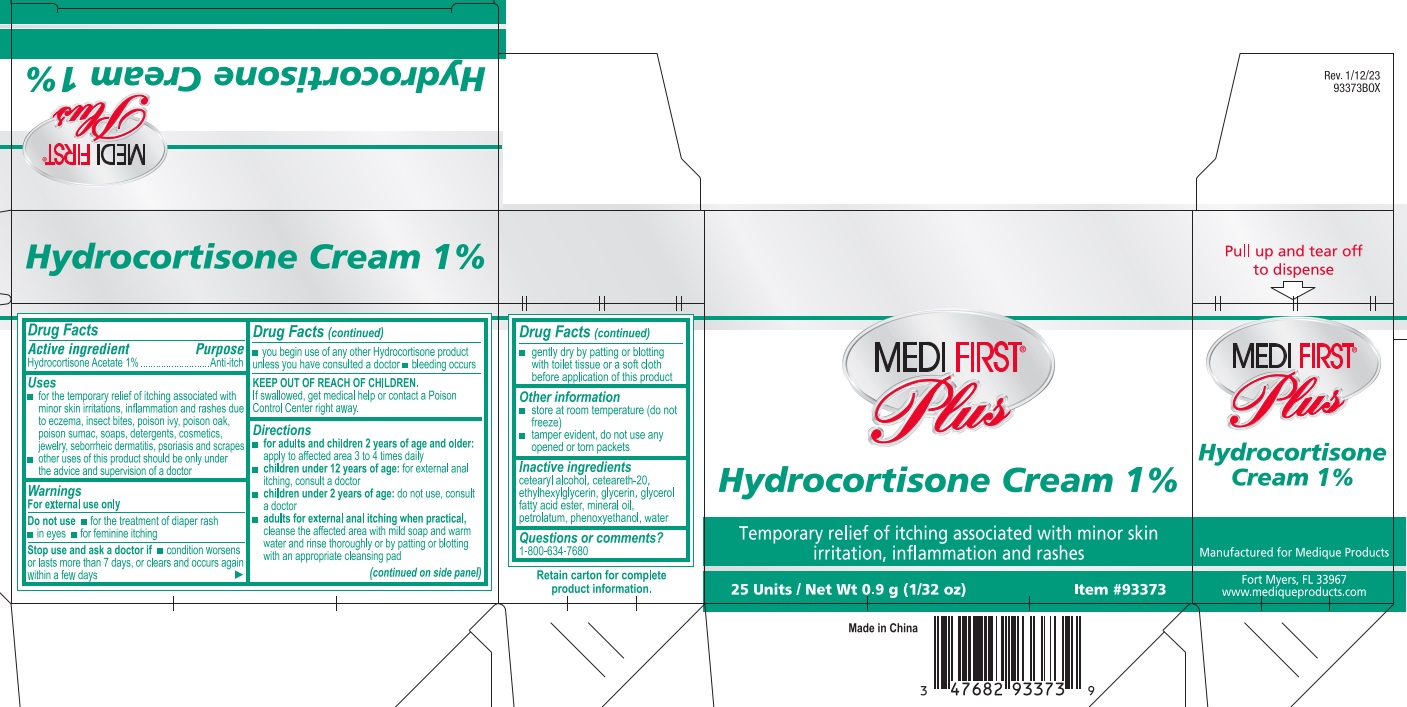 DRUG LABEL: Medi-First Plus Hydrocortisone 1%
NDC: 47682-981 | Form: CREAM
Manufacturer: Unifirst First Aid Corporation
Category: otc | Type: HUMAN OTC DRUG LABEL
Date: 20251024

ACTIVE INGREDIENTS: HYDROCORTISONE ACETATE 10 mg/1 g
INACTIVE INGREDIENTS: GLYCERYL MONOSTEARATE; POLYOXYL 20 CETOSTEARYL ETHER; WATER; CETOSTEARYL ALCOHOL; ETHYLHEXYLGLYCERIN; GLYCERIN; PHENOXYETHANOL; MINERAL OIL; PETROLATUM

Medi-First Hydrocortisone Cream 1%

Drug Facts

Active ingredient

Hydrocortisone Acetate 1%

Purpose

Anti-itch

Uses

- for the temporary relief of itching associated with minor skin irritations and rashes due to eczema, insect bites, poison ivy, poison oak, poison sumac, soaps, detergents, psoriasis and scrapes
- other uses of this product should be only under the advice and supervision of a doctor

Warnings

For external use only

Do not use

- for the treatment of diaper rash
- in eyes
- for feminine itching

Stop use and ask a doctor if

- condition worsens or lasts more than 7 days, or clears up and occurs again within a few days
- you begin use of any other Hydrocortisone product unless you have consulted a doctor
- bleeding occurs

Keep out of reach of children.

If swallowed, get medical help or contact a Poison Control Center right away.

Directions

- for adults and children 2 years of age and older: apply to the affected area 3 to 4 times daily
- children under 12 years of age: for external anal itching, consult a doctor
- children under 2 years of age: do not use, consult a doctor
- adults for external anal itching when practical, cleanse the affected area with mild soap and warm water and rinse thoroughly or by patting or blotting with appropriate cleansing pad
- gently dry by patting or blotting with toilet tissue or a soft cloth before application of this product

Other information

- store at room temperature (do not freeze)
- tamper evident. Do not use any opened or torn packets

Inactive ingredients

cetearyl alcohol, ceteareth-20, ethylhexylglycerin, glycerin, glyceryl fatty acid ester, mineral oil,
petrolatum, phenoxyethanol, water

Questions or comments? 1-800-634-7680

PACKAGE LABEL

Medi-First®

1% Hydrocorisone Cream

Temporary relief of itching associated with minor skin irritation, inflamation and rashes

Item #21173

Net Wt. 0.9 g (1/32 oz) Packets/ 25 per box

Made in China

PACKAGE LABEL

Medi-First® Plus

Hydrocortisone Cream 1%

Temporary relief of itching associated with minor skin irritation, inflamation and rashes

25 Units / Net Wt 0.9 g (1/32 oz)

Item #93373

Made in China